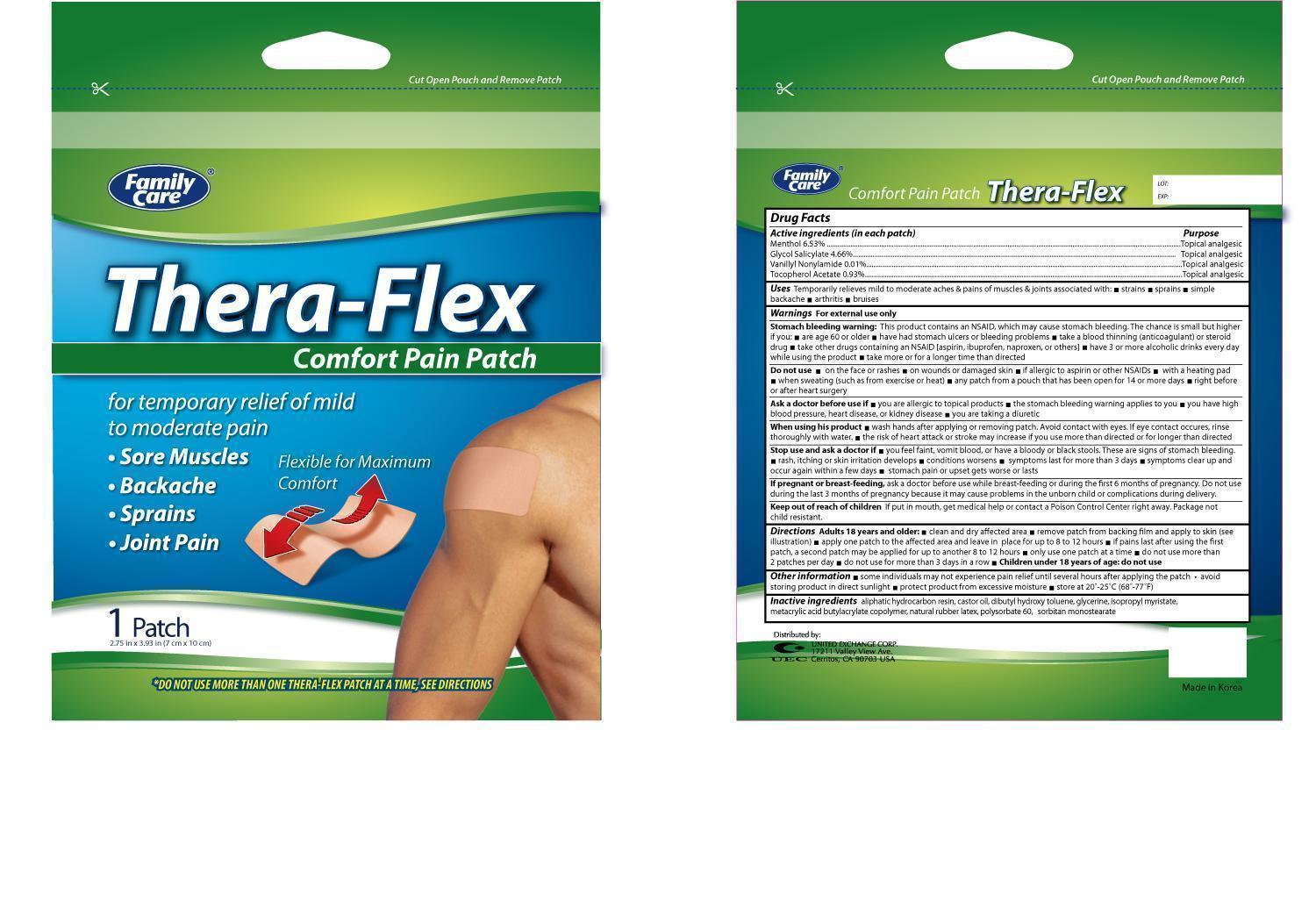 DRUG LABEL: Family Care Thera Flex
NDC: 65923-012 | Form: PATCH
Manufacturer: United Exchange Corp.
Category: otc | Type: HUMAN OTC DRUG LABEL
Date: 20131115

ACTIVE INGREDIENTS: MENTHOL 6.53 mg/100 mg; GLYCOL SALICYLATE 4.66 mg/100 mg; NONIVAMIDE .01 mg/100 mg; ALPHA-TOCOPHEROL ACETATE .93 mg/100 mg
INACTIVE INGREDIENTS: CASTOR OIL; GLYCERIN; ISOPROPYL MYRISTATE; NATURAL LATEX RUBBER; POLYSORBATE 60; SORBITAN MONOSTEARATE

Active Ingredients (in each patch) Purpose

Menthol 6.53%........................................................................................... Topical analgesic

Glycol Salicylate 4.66%............................................................................... Topical analgesic

Nonivamide 0.01%...................................................................................... Topical analgesic

Tocopherol Acetate 0.93%............................................................................ Topical analgesic

PURPOSE

Uses: Temporarily relieves mild to moderate aches & pain of muscles & joints associated with:

- strains
- sprains
- simple backache
- arthritis
- bruises

WARNINGS

For external use only

Stomach bleeding warning: This product contains an NSAID, which may cause stomach bleeding. The chance is small but higher if you:

- are 60 or older
- have had stomach ulcers or bleeding problems
- take a blood thinning (anticoagulant) or steroid drug
- take other drugs containing an NSAID (aspirin, ibuprofen, naproxen, or others)
- have 3 or more alcoholic drinks every day while using the product
- take more or for a longer time than directed

Do not use:

- on the face or rashes
- on wounds or damaged skin
- if allergic to aspirin or other NSAIDs
- with a heating pad
- when sweating (such as from exercise or heat)
- any patch from a pouch that has been open for 14 or more days
- right before or after heart surgery

Ask a doctor before use:

- if you are allergic to topical products
- the stomach bleeding warning applies to your
- you have high blood pressure, heart disease, or kidney disease
- you are taking a diuretic

When using this prdouct

- wash hands after applying or removing patch. Avoid contact with eyes. If eye contact occures, rinse thoroughly with water
- the risk of hear attack or stroke may increase if you use more than directed or for longer than directed

Stop use and ask a doctor if:

- you feel faint, vomit blood, or have bloody or black stools. These are signs of stomach bleeding
- rash, itching or skin irritation develops
- conditions worsens
- symptoms last for more than 3 days
- symptoms clear up and occur again within a few days
- stomach pain or upset gets worse or lasts

PREGNANCY OR BREAST FEEDING

If pregnant or breast-feeding, ask a doctor before use while breast-feeding or during the first 6 months of pregnancy. Do not use during the last 3 months of pregnancy because it may cause problems in the unborn child or complcations during delivery.

KEEP OUT OF REACH OF CHILDREN

If put in mouth, get medical help or contact a Poision Contol Center right away. Package not child resistant.

INDICATIONS AND USAGE

Directions: Adult 18 years and older

- clean and dry affected area
- remove patch from backing film and apply to skin (see illustration)
- apply one patch to the affected area and leave in place for up to 8 to 12 hours
- if pains last after using the first patch, a second patch may be applied for up to another 8 to 12 hours
- only use on patch at a time
- do not use more than 2 patches per day
- do not use for more than 3 days in a row
- Children under 18 years of age: do not use

Other Information

- some individuals may not experience pain relief until several hours after applying the patch
- avoid storing product in direct sunlight
- protect product from excessive moisture
- store at 20°-25°C (68°-77°F)

INACTIVE INGREDIENT

Inactive ingredients: aliphatic hydrocarbon resin, castor oil, dibutyl hydroxy toluene, glycerine, isopropyl myristate, metacrylic acid butylacrylate copolymer, natural rubber latex, polysorbate 60, sorbitan monostearate

DOSAGE AND ADMINISTRATION

DISTRIBUTED BY:

UNITED EXCHANGE CORP.

17211 VALLEY VIEW AVE.

CERRITOS, CA 90703 USA